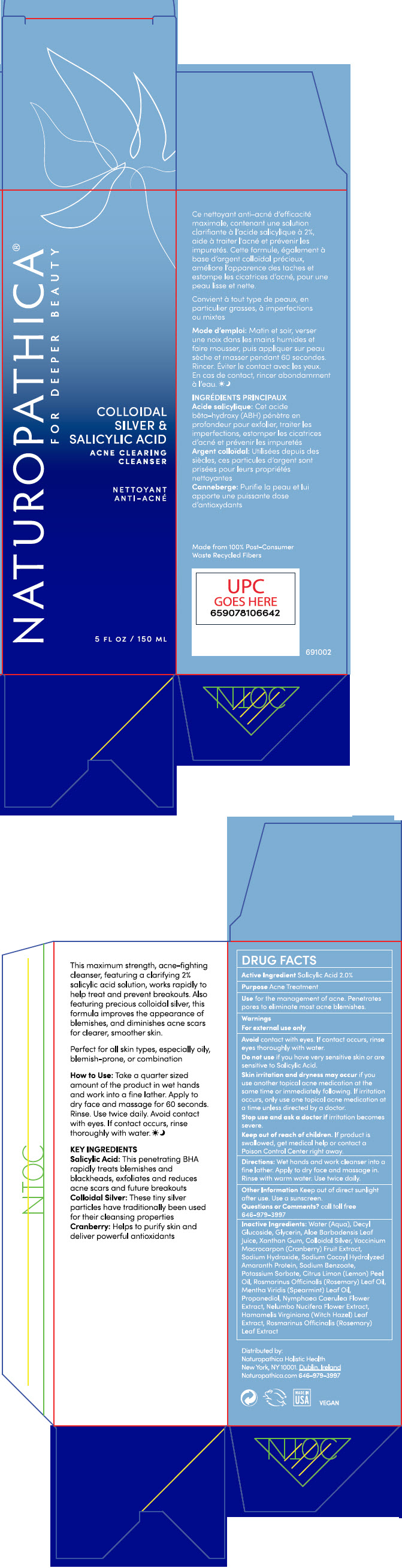 DRUG LABEL: NATUROPATHICA COLLOIDAL SILVER AND SALICYLIC ACID ACNE CLEARING CLEANSER
NDC: 64657-001 | Form: GEL
Manufacturer: Naturopathica Holistic Health
Category: otc | Type: HUMAN OTC DRUG LABEL
Date: 20240530

ACTIVE INGREDIENTS: SALICYLIC ACID 2 g/100 mL
INACTIVE INGREDIENTS: WATER; DECYL GLUCOSIDE; GLYCERIN; ALOE VERA LEAF; XANTHAN GUM; SILVER; CRANBERRY; SODIUM HYDROXIDE; SODIUM BENZOATE; POTASSIUM SORBATE; LEMON OIL, COLD PRESSED; ROSEMARY OIL; SPEARMINT OIL; PROPANEDIOL; NYMPHAEA CAERULEA FLOWER; NELUMBO NUCIFERA FLOWER; HAMAMELIS VIRGINIANA LEAF; ROSEMARY

NATUROPATHICA®COLLOIDAL SILVER AND SALICYLIC ACID ACNE CLEARING CLEANSER

DRUG FACTS

ACTIVE INGREDIENTS

SALICYLIC ACID 2.0%

PURPOSE

ACNE TREATMENT

Use

for the management of acne.

Penetrates pores to eliminate most acne blemishes.

Warnings

For external use only

When using this product

- Avoid contact with eyes. If contact occurs, rinse eyes thoroughly with water.
- Do not use if you have very sensitive skin or are sensitive to Salicylic Acid.
- skin irritation and dryness may occur if you use another topical acne medication at the same time or immediately following. If irritation occurs, only use one topical acne medication at a time unless directed by a doctor.

Stop use and ask a doctor

If irritation becomes severe.

Keep out of reach of children.

If swallowed, get medical help or contact a Poison Control Center right away.

Directions

Take a quarter sized amount of the product in wet hands and work into a fine lather. Apply to dry face and massage for 60 seconds. Rinse with warm water and pat the skin dry. Use twice daily.

STORAGE AND HANDLING

Keep out of direct sunlight after use. Use a sunscreen.

INACTIVE INGREDIENTS

WATER(AQUA), DECYL GLUCOSIDE, GLYCERIN, ALOE BARBADENSIS LEAF JUICE,XANTHAN GUM, COLLOIDAL SILVER, VACCINIUM MACROCARPON (CRANBERRY) FRUIT EXTRACT, SODIUM HYDROXIDE, SODIUM COCOYL HYDROLYZED AMARANTH PROTEIN, SODIUM BENZOATE, POTASSIUM SORBATE, CITRUS LIMON (LEMON) PEEL OIL , ROSMARINUS OFFICINALIS (ROSEMARY) LEAF OIL, MENTHA VIRIDIS(SPEARMINT) LEAF OIL, PROPANEDIOL, NYMPHAEA CAERULEA FLOWER EXTRACT, NELUMBO NUCIFERA FLOWER EXTRACT, HAMAMELIS VIRGINIANA (WITCH HAZEL) LEAF EXTRACT, ROSMARINUS OFFICINALIS (ROSEMARY) LEAF EXTRACT.

CERTIFIED ORGANIC

Questions or Comments?

call toll free 646-979-3997

Distributed by:
Naturopathica Holistic Health
New York, NY 10001. Dublin, Ireland

PRINCIPAL DISPLAY PANEL - 150 mL Bottle Carton

NATUROPATHICA®
FOR DEEPER BEAUTY

COLLOIDAL
SILVER &
SALICYCLIC ACID

ACNE CLEARING
CLEANSER

5 FL OZ / 150 ML